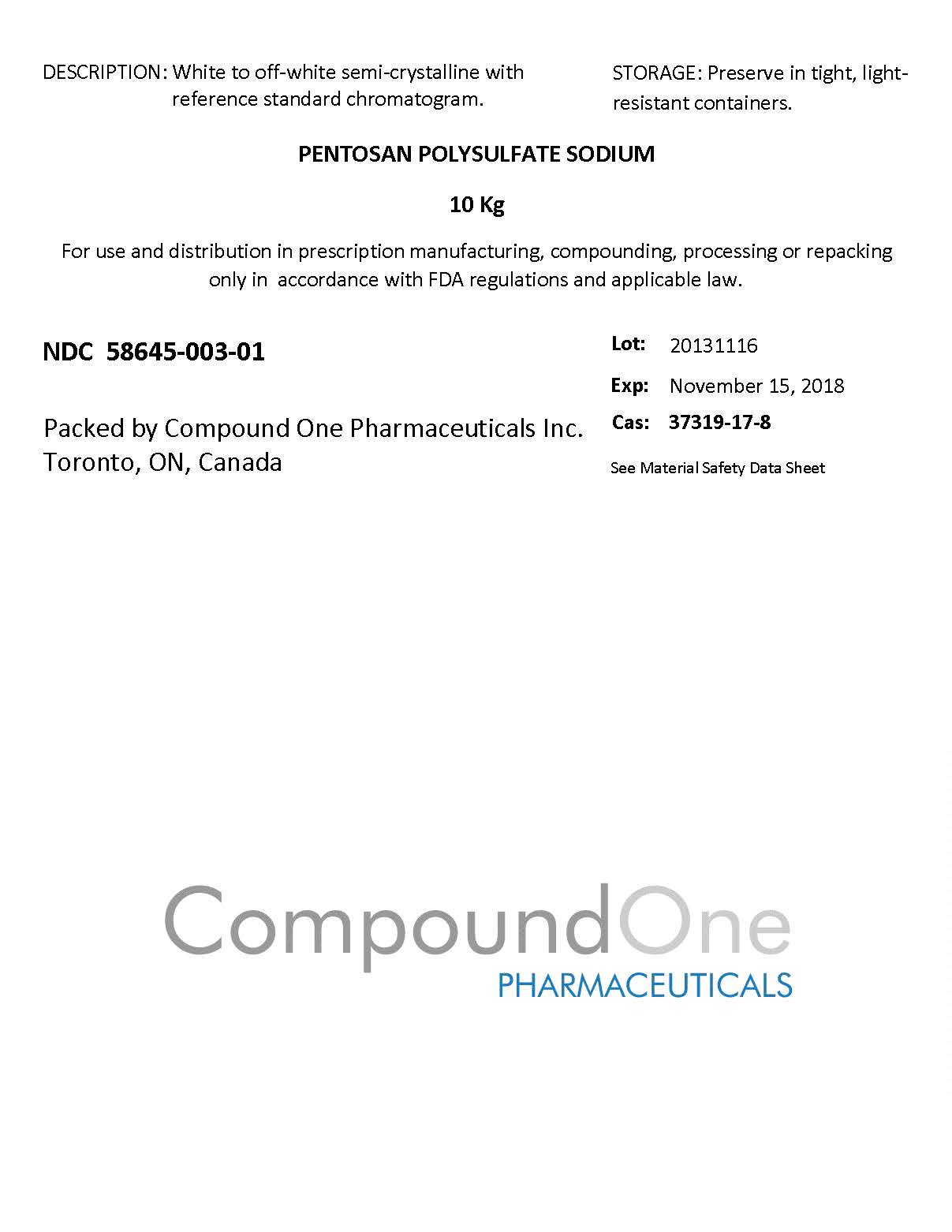 DRUG LABEL: PENTOSAN
                
                
NDC: 58645-003 | Form: POWDER
Manufacturer: Compound One Pharmaceuticals Inc.
Category: other | Type: BULK INGREDIENT
Date: 20140106

ACTIVE INGREDIENTS: PENTOSAN POLYSULFATE SODIUM 1 g/1 g

Drug Facts